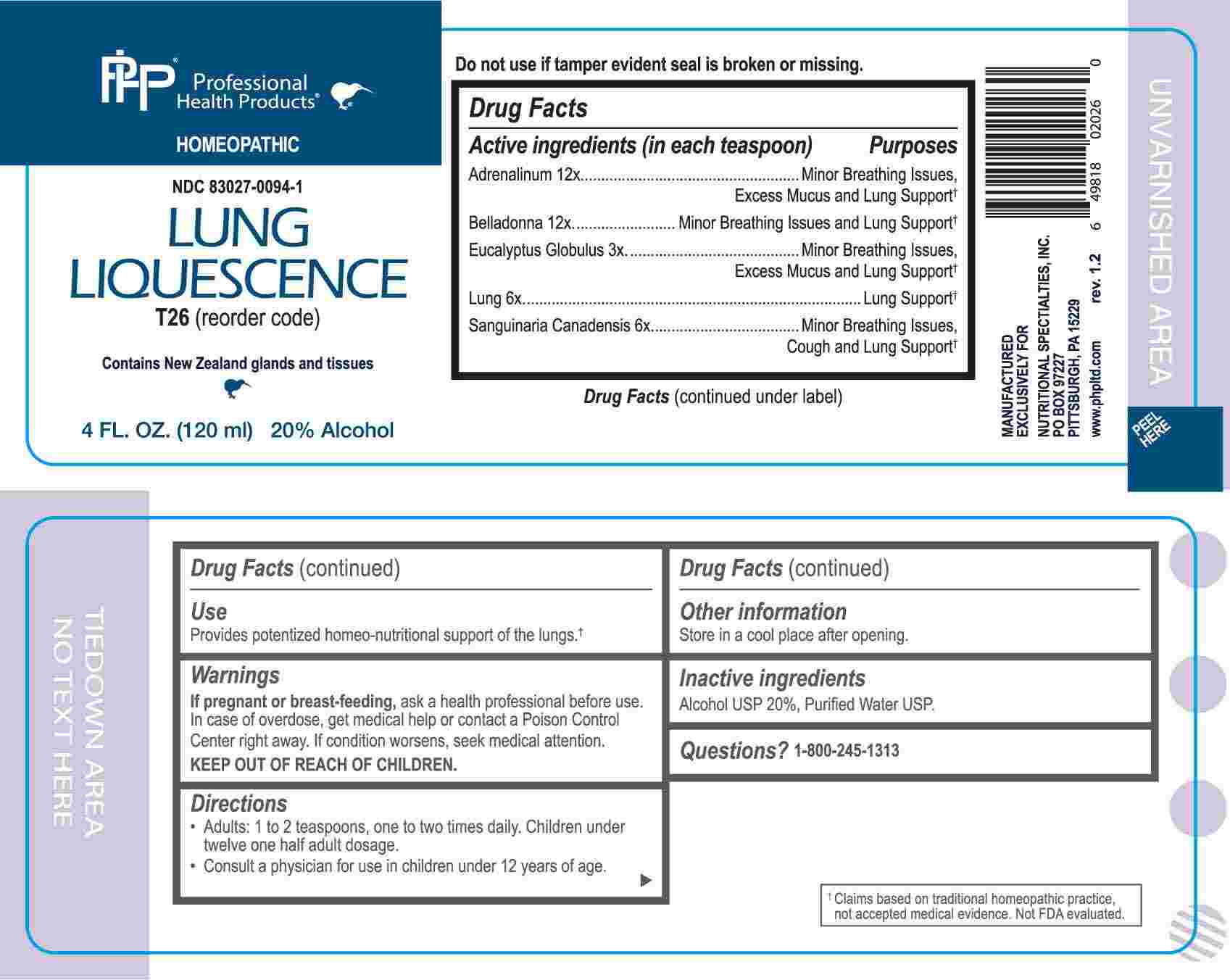 DRUG LABEL: Lung Liquescence
NDC: 83027-0094 | Form: LIQUID
Manufacturer: Nutritional Specialties, Inc.
Category: homeopathic | Type: HUMAN OTC DRUG LABEL
Date: 20240805

ACTIVE INGREDIENTS: EUCALYPTUS GLOBULUS LEAF 3 [hp_X]/1 mL; BEEF LUNG 6 [hp_X]/1 mL; SANGUINARIA CANADENSIS ROOT 6 [hp_X]/1 mL; EPINEPHRINE 12 [hp_X]/1 mL; ATROPA BELLADONNA 12 [hp_X]/1 mL
INACTIVE INGREDIENTS: WATER; ALCOHOL

DRUG FACTS:

ACTIVE INGREDIENTS:

(in each teaspoon) Adrenalinum 12X, Belladonna 12X, Eucalyptus Globulus 3X, Lung 6X, Sanguinaria Canadensis 6X.

PURPOSE:

Adrenalinum – Miner Breathing Issues, Excess Mucus and Lung Support,† Belladonna – Minor Breathing Issues and Lung Support,† Eucalyptus Globulus - Miner Breathing Issues, Excess Mucus and Lung Support,† Lung – Lung Support,† Sanguinaria Canadensis – Minor Breathing Issues, Cough and Lung Support.†

†Claims based on traditional homeopathic practice, not accepted medical evidence. Not FDA evaluated.

USES:

Provides potentized homeo-nutritional support of the lungs.†

†Claims based on traditional homeopathic practice, not accepted medical evidence. Not FDA evaluated.

WARNINGS:

If pregnant or breast-feeding, ask a health professional before use.

In case of overdose, get medical help or contact a Poison Control Center right away.

If condition worsens, seek medical attention.

KEEP OUT OF REACH OF CHILDREN

Do not use if tamper evident seal is broken or missing.

Store in a cool place after opening

KEEP OUT OF REACH OF CHILDREN:

In case of overdose, get medical help or contact a Poison Control Center right away.

DIRECTIONS:

• Adults: 1 to 2 teaspoons, one to two times daily. Children under twelve one half adult dosage.

Consult a physician for use in children under 12 years of age.

INACTIVE INGREDIENTS:

Alcohol USP 20%, Purified Water USP.

QUESTIONS:

MANUFACTURED EXCLUSIVELY FOR

NUTRITIONAL SPECIALTIES, INC.

PO BOX 97227

PITTSBURG, PA 15229

www.phpltd.com

PACKAGE LABEL DISPLAY:

Professional

Health Products

HOMEOPATHIC

NDC 83027-0094-1

LUNG

LIQUESCENCE

4 FL. OZ (120 ml)